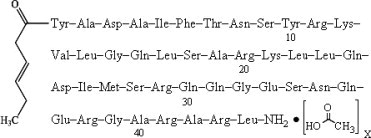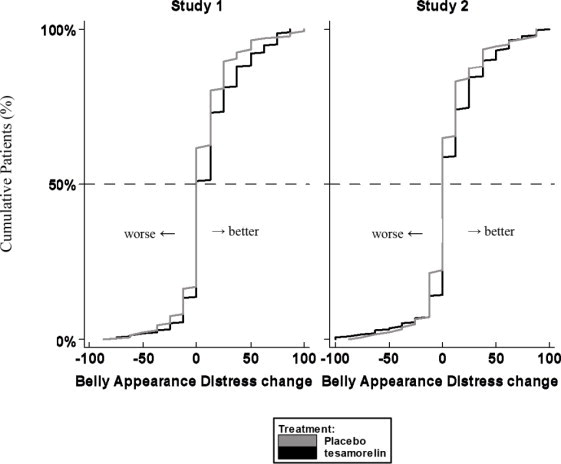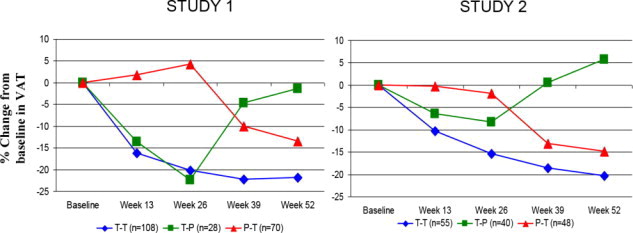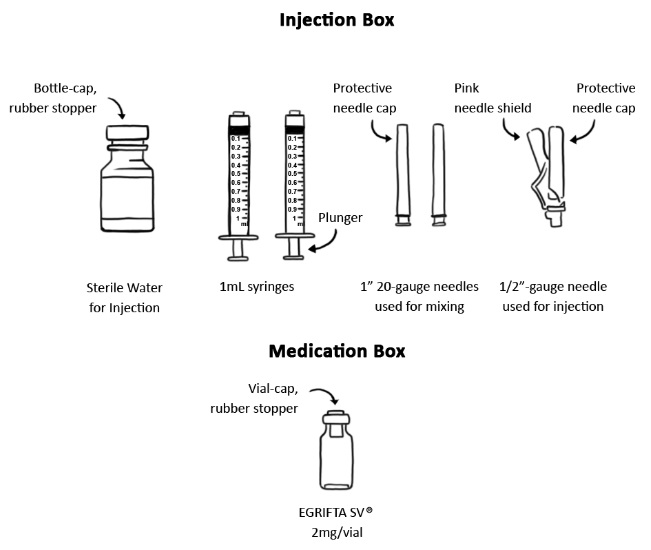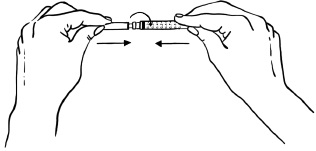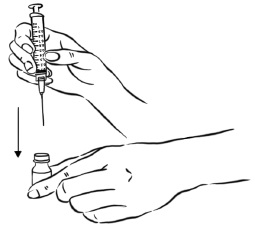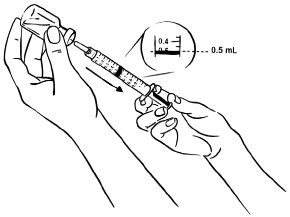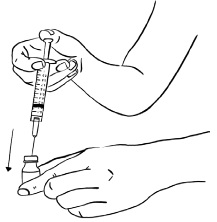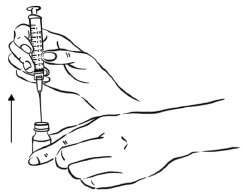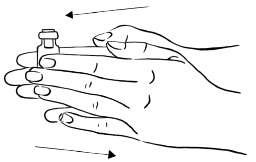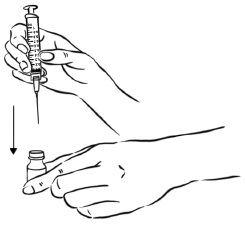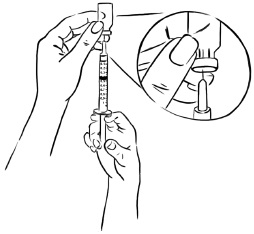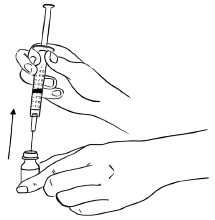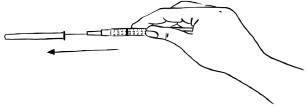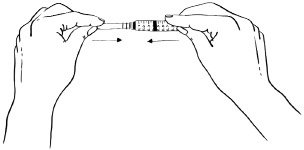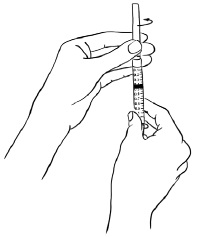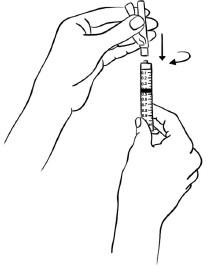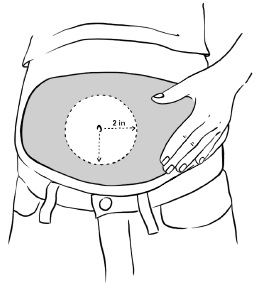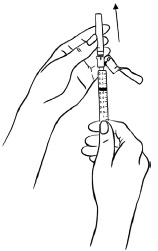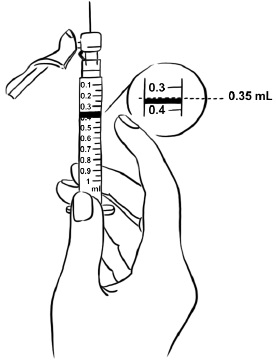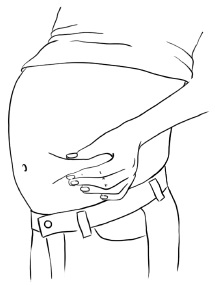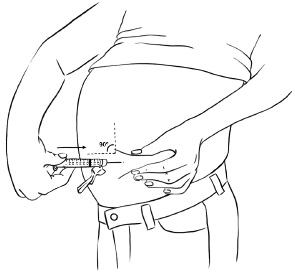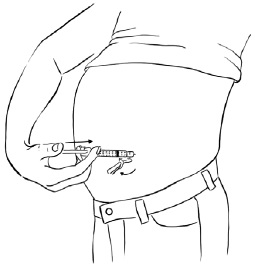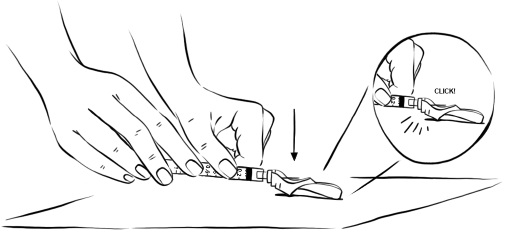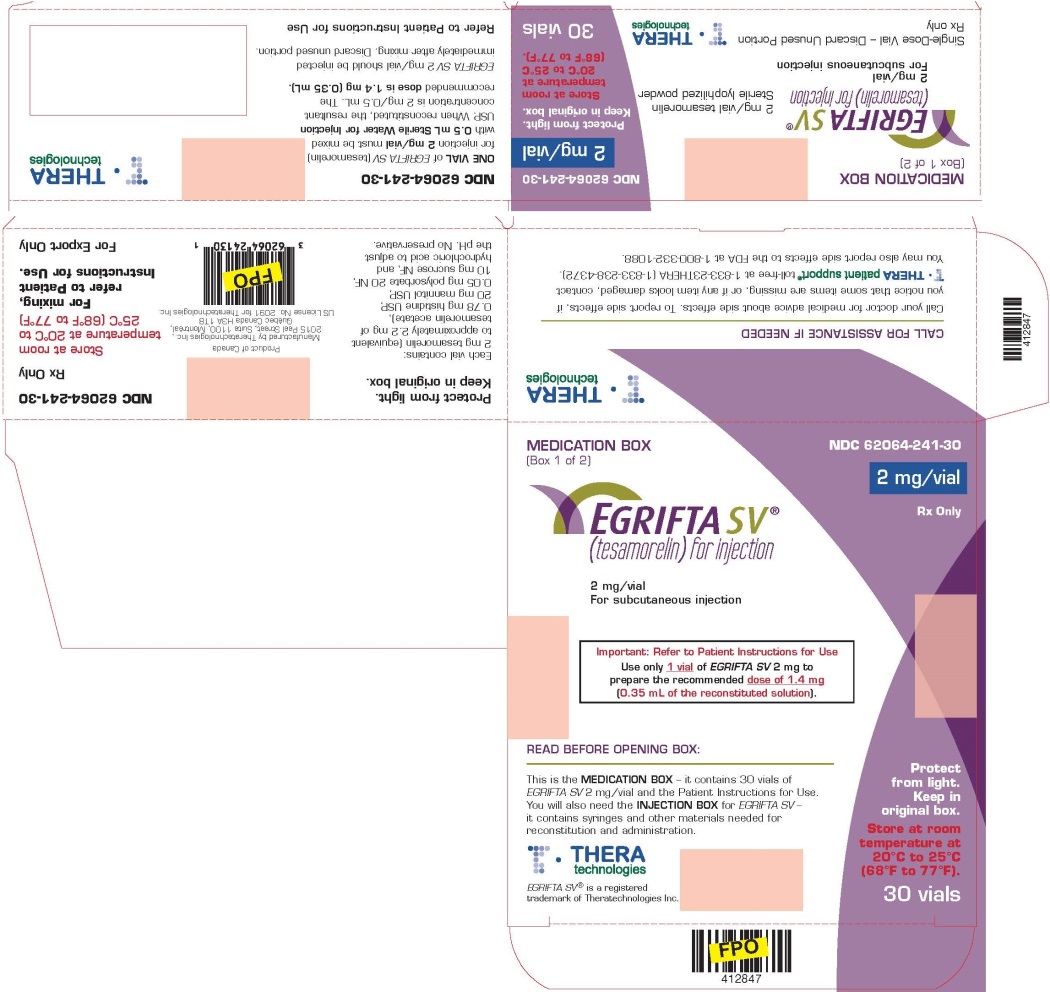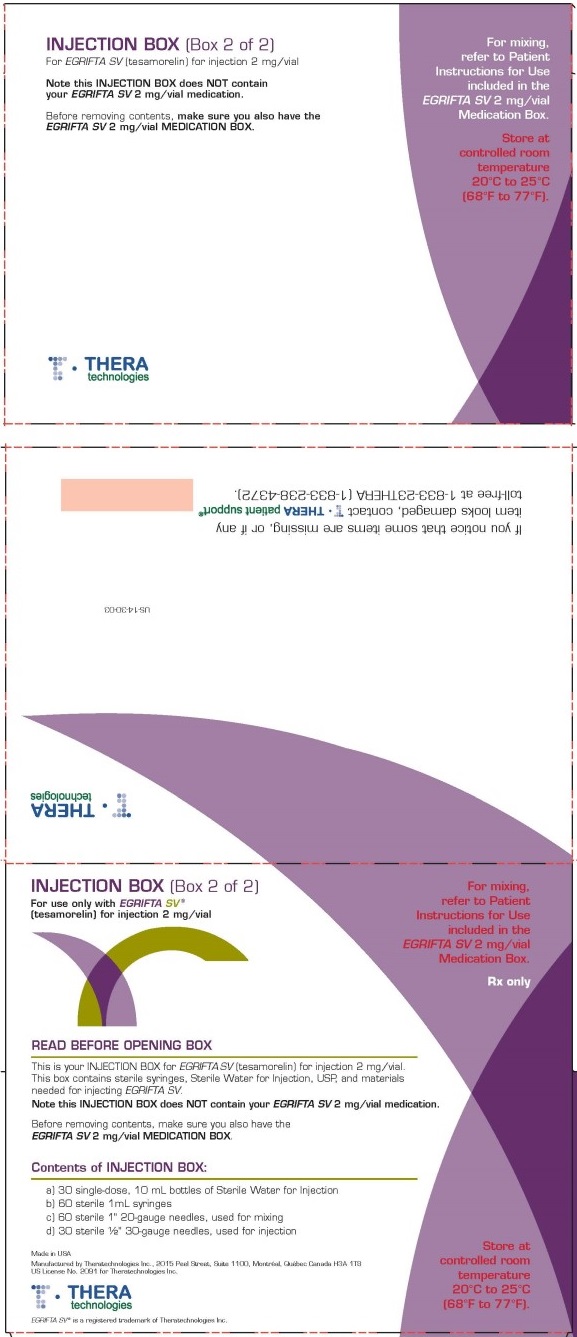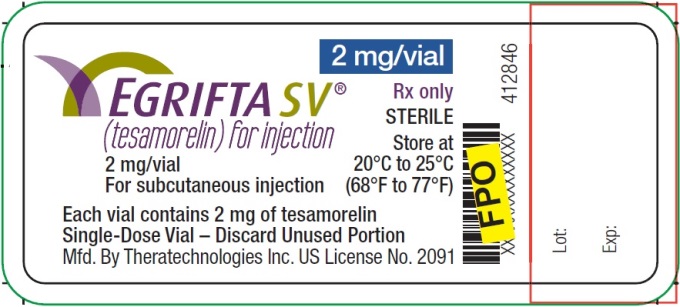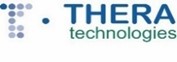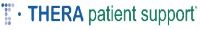 DRUG LABEL: EGRIFTA SV
NDC: 62064-241 | Form: KIT | Route: SUBCUTANEOUS
Manufacturer: Theratechnologies Inc.
Category: prescription | Type: HUMAN PRESCRIPTION DRUG LABEL
Date: 20251223

ACTIVE INGREDIENTS: TESAMORELIN ACETATE 2 mg/0.5 mL
INACTIVE INGREDIENTS: MANNITOL 20 mg/0.5 mL; SUCROSE 10 mg/0.5 mL; HISTIDINE 0.78 mg/0.5 mL; POLYSORBATE 20 0.05 mg/0.5 mL; WATER

HIGHLIGHTS OF PRESCRIBING INFORMATION

These highlights do not include all the information needed to use EGRIFTA SV safely and effectively. See full prescribing information for EGRIFTA SV.
EGRIFTA SV® (tesamorelin) for injection, for subcutaneous use
Initial U.S. Approval: 2010

1 INDICATIONS AND USAGE

EGRIFTA SV is a growth hormone-releasing factor (GHRF) analog indicated for the reduction of excess abdominal fat in HIV-infected adult patients with lipodystrophy. (1)

Limitations of use:

- Long-term cardiovascular safety of EGRIFTA SV has not been established. (1)
- Not indicated for weight loss management. (1)
- There are no data to support improved compliance with anti-retroviral therapies in HIV-positive patients taking EGRIFTA SV. (1)

2 DOSAGE AND ADMINISTRATION

- The recommendations in this prescribing information only apply to EGRIFTA SV (tesamorelin) for injection 2 mg per vial formulation. For recommendations for tesamorelin for injection 1 mg per vial formulation, see the EGRIFTA prescribing information. These two formulations and strengths have differences in the dosage, the number of vials required to prepare a dose, reconstitution instructions, and storage requirements. (2.1).
- The dose of EGRIFTA SV is 1.4 mg (0.35 mL of the reconstituted solution) injected subcutaneously once daily. (2.1)
- Inject EGRIFTA SV into the abdomen, rotating injection sites. (2.1,5.6)
- Use only the diluent provided, Sterile Water for Injection, to reconstitute EGRIFTA SV. (2.2)
- Reconstitute one vial of lyophilized powder with 0.5 mL of diluent. Mix by rolling the vial gently in your hands for 30 seconds. Do not shake. (2.2)
- Inspect the reconstituted vial visually for particulate matter and discoloration. Use only if the solution is clear, colorless and without particulate matter. (2.2)
- Administer 0.35 mL of EGRIFTA SV immediately following reconstitution and throw away any unused solution and diluent. (2.2)

3 DOSAGE FORMS AND STRENGTHS

- For injection: 2 mg in a single-dose vial with a diluent of 10 mL of Sterile Water for Injection (3)

4 CONTRAINDICATIONS

EGRIFTA SV is contraindicated in:

- Patients with disruption of the hypothalamic-pituitary axis (4)
- Patients with active malignancy (4)
- Patients with known hypersensitivity to tesamorelin or excipients in EGRIFTA SV (4)
- Pregnancy (4)

5 WARNINGS AND PRECAUTIONS

- Increased risk of neoplasms: Preexisting malignancy should be inactive and its treatment complete prior to starting EGRIFTA SV. Discontinue EGRIFTA SV if there is any evidence of recurrent malignancy. (5.1)
- Elevated IGF-1: EGRIFTA SV stimulates GH production and increases serum IGF-1, a growth factor. The effects of prolonged elevations in IGF-1 levels are unknown. Monitor IGF-1 levels during EGRIFTA SV therapy. Consider discontinuing in patients with persistent elevations. (5.2)
- Fluid retention: May occur with EGRIFTA SV and may include edema, arthralgia, and carpal tunnel syndrome. (5.3)
- Glucose intolerance or diabetes mellitus: May develop with EGRIFTA SV use. Evaluate glucose prior to and during therapy. (5.4)
- Hypersensitivity reactions: Have occurred in clinical trials. Advise patients to seek immediate medical attention and discontinue treatment if suspected. (5.5)
- Increased mortality in patients with acute critical illness: Consider discontinuation in critically ill patients. (5.7)

6 ADVERSE REACTIONS

Most commonly reported adverse reactions (>5%): Arthralgia, injection site erythema, injection site pruritus, pain in extremity, peripheral edema, and myalgia. (6.1)

To report SUSPECTED ADVERSE REACTIONS, contact THERA patient support® toll free at 1-833-23THERA (1-833-238-4372) or FDA at 1-800-FDA-1088 or www.fda.gov/medwatch

7 DRUG INTERACTIONS

- Cytochrome P450-metabolized drugs: Monitor patients for potential interactions when administering with EGRIFTA SV. (7.1)
- Glucocorticoids: Patients receiving glucocorticoid replacement for previously diagnosed hypoadrenalism may require an increase in maintenance or stress doses following initiation of EGRIFTA SV. (7.2)

8 USE IN SPECIFIC POPULATIONS

- Lactation: HIV-1 infected mothers should not breastfeed to avoid potential postnatal transmission of HIV-1. (8.2)

FULL PRESCRIBING INFORMATION

1 INDICATIONS AND USAGE

EGRIFTA SV is indicated for the reduction of excess abdominal fat in HIV-infected adult patients with lipodystrophy.

Limitations of Use:

- Long-term cardiovascular safety of EGRIFTA SV has not been established. Consider risk/benefit of continuation of treatment in patients who have not had a reduction in visceral adipose tissue.
- EGRIFTA SV is not indicated for weight loss management as it has a weight neutral effect.
- There are no data to support improved compliance with anti-retroviral therapies in HIV-positive patients taking EGRIFTA SV.

2 DOSAGE AND ADMINISTRATION

2.1 Dosage and Administration

• The dosage and administration recommendations in this prescribing information only apply to EGRIFTA SV (tesamorelin) for injection 2 mg per vial formulation. For dosage and administration recommendations for tesamorelin for injection 1 mg per vial formulation, see the EGRIFTA prescribing information. These two formulations and strengths have differences in the dosage, the number of vials required to prepare a dose, reconstitution instructions, and storage requirements.
• The dose of EGRIFTA SV is 1.4 mg, 0.35 mL of the reconstituted solution [see Dosage and Administration (2.2)], injected subcutaneously once daily.
• Inject EGRIFTA SV into the abdomen. Rotate injection sites to different areas of the abdomen [see Warnings and Precautions (5.5)]. Do not inject into scar tissue, bruises or the navel.

2.2 Reconstitution Procedure

• Instruct patients to read the Instructions for Use enclosed in the EGRIFTA SV Medication Box.
• Use only the diluent provided, Sterile Water for Injection, to reconstitute EGRIFTA SV.
• Reconstitute 1 vial of EGRIFTA SV lyophilized powder with 0.5 mL of diluent (2 mg per 0.5 mL). Mix by rolling the vial gently in your hands for 30 seconds. Do not shake.
• Parenteral drug products should be inspected visually for particulate matter and discoloration prior to administration, whenever solution and container permit. Use only if the solution is clear, colorless and without particulate matter.
• Administer 0.35 mL of EGRIFTA SV immediately following reconstitution and throw away any unused solution and diluent. If not used immediately, discard the reconstituted solution. Do not freeze or refrigerate the reconstituted solution.

3 DOSAGE FORMS AND STRENGTHS

For injection: 2 mg of tesamorelin as a white to off-white lyophilized powder in a single-dose vial and a diluent of 10 mL of Sterile Water for Injection.

4 CONTRAINDICATIONS

EGRIFTA SV is contraindicated in:

- Patients with disruption of the hypothalamic-pituitary axis due to hypophysectomy, hypopituitarism, pituitary tumor/surgery, head irradiation or head trauma.
- Patients with active malignancy. Any preexisting malignancy should be inactive and its treatment complete prior to instituting therapy [see Warnings and Precautions (5.1)].
- Patients with known hypersensitivity to tesamorelin or the excipients in EGRIFTA SV [see Warnings and Precautions (5.5)].
- Pregnant women because modifying visceral adipose tissue offers no benefit in a pregnant woman and could result in fetal harm [see Use in Specific Populations (8.1)].

5 WARNINGS AND PRECAUTIONS

5.1 Increased Risk of Neoplasms

New Malignancy

Carefully consider the decision to start treatment with EGRIFTA SV based on the increased background risk of malignancies in HIV-positive patients.

Active Malignancy

EGRIFTA SV induces the release of endogenous growth hormone (GH), a known growth factor. Do not treat patients with active malignancy with EGRIFTA SV [see Contraindications (4)].

History of Malignancy

For patients with a history of non-malignant neoplasms, initiate EGRIFTA SV therapy after careful evaluation of the potential benefit of treatment. For patients with a history of treated and stable malignancies, initiate EGRIFTA SV therapy only after careful evaluation of the potential benefit of treatment relative to the risk of re-activation of the underlying malignancy. Discontinue EGRIFTA SV if there is any evidence of recurrent malignancy.

5.2 Elevated IGF-1 Levels

EGRIFTA SV stimulates GH production and increases serum IGF-1, a growth factor. The effects of prolonged elevations in IGF-1 levels are unknown. Monitor IGF-1 levels during EGRIFTA SV therapy. Consider discontinuing EGRIFTA SV in patients with persistent elevations of IGF-1 levels (e.g., >3 SDS), particularly if the efficacy response is not robust.

Among patients who received EGRIFTA for 26 weeks, 47% had IGF-1 levels greater than 2 standard deviation scores (SDS), and 36% had SDS >3, with this effect seen as early as 13 weeks of treatment. Among those patients who remained on EGRIFTA for a total of 52 weeks, at the end of treatment, 34% had IGF-1 SDS >2 and 23% had IGF-1 SDS >3.

5.3 Fluid Retention

Fluid retention may occur during EGRIFTA SV therapy and is thought to be related to the induction of GH secretion. This manifests as increased tissue turgor and musculoskeletal discomfort resulting in adverse reactions (e.g. edema, arthralgia, and carpal tunnel syndrome) which are either transient or resolve with discontinuation of treatment.

5.4 Glucose Intolerance or Diabetes Mellitus

EGRIFTA SV treatment can result in glucose intolerance. During clinical trials, the percentages of patients with elevated HbA1c (≥ 6.5%) from baseline to Week 26 were 5% and 1% in the EGRIFTA and placebo groups, respectively. An increased risk of developing diabetes with EGRIFTA (HbA1c level ≥ 6.5%) relative to placebo was observed [intent-to-treat hazard odds ratio of 3.3 (CI 1.4, 9.6)].

Evaluate glucose status prior to initiating EGRIFTA SV. Monitor all patients treated with EGRIFTA SV periodically to diagnose those who develop impaired glucose tolerance or diabetes. If patients treated with EGRIFTA SV develop glucose intolerance or diabetes, consider discontinuing EGRIFTA SV in patients who do not show a clear efficacy response.

EGRIFTA SV increases IGF-1, monitor patients with diabetes who are receiving treatment with EGRIFTA SV at regular intervals for potential development or worsening of retinopathy.

5.5 Hypersensitivity Reactions

Hypersensitivity reactions occurred in 4% of patients treated with EGRIFTA in clinical trials. Reactions included pruritus, erythema, flushing, urticaria, and rash. In cases of suspected hypersensitivity reactions, advise patients to seek prompt medical attention and immediately discontinue treatment with EGRIFTA SV.

5.6 Injection Site Reactions

EGRIFTA SV treatment may cause injection site reactions, including injection site erythema, pruritus, pain, irritation, and bruising. The incidence of injection site reactions was 25% in EGRIFTA treated patients and 14% in placebo-treated patients during the first 26 weeks of treatment in clinical trials. Rotate injection sites to different areas of the abdomen to decrease injection site reactions [see Dosage and Administration (2.1)].

5.7 Increased Mortality in Patients with Acute Critical Illness

Increased mortality in patients with acute critical illness due to complications following open heart surgery, abdominal surgery or multiple accidental trauma, or those with acute respiratory failure has been reported after treatment with pharmacologic amounts of growth hormone. EGRIFTA SV is a growth hormone-releasing hormone (GHRH) and since it stimulates growth hormone production, consider discontinuing EGRIFTA SV in critically ill patients.

6 ADVERSE REACTIONS

The following important adverse reactions are also described elsewhere in the labeling:

- Increased risk of neoplasms [see Warnings and Precautions (5.1)]
- Elevated IGF-1 levels [see Warnings and Precautions (5.2)]
- Fluid retention [see Warnings and Precautions (5.3)]
- Glucose intolerance or diabetes mellitus [see Warnings and Precautions (5.4)]
- Hypersensitivity reactions [see Warnings and Precautions (5.5)]
- Injection site reactions [see Warnings and Precautions (5.6)]

6.1 Clinical Trial Experience

Because clinical trials are conducted under widely varying conditions, adverse reaction rates observed in the clinical trials of a drug cannot be directly compared to rates in the clinical trials of another drug and may not reflect the rates observed in practice.

The safety of EGRIFTA SV (2 mg/vial formulation) has been established based on clinical trials conducted with EGRIFTA (1 mg/vial formulation). Adverse reactions for the 1.4 mg dose (2 mg/vial formulation) of EGRIFTA SV are expected to be similar to those observed with the 2 mg dose (1 mg/vial formulation) of EGRIFTA [see Clinical Pharmacology (12.3)].

Seven hundred and forty (740) HIV-infected patients with lipodystrophy and excess abdominal fat were treated with EGRIFTA in clinical trials; of these, 543 received EGRIFTA during the initial 26-week placebo-controlled phase.

The most commonly reported adverse reactions were hypersensitivity reactions (e.g., rash, urticaria), edema-related reactions (e.g., arthralgia, extremity pain, peripheral edema, and carpal tunnel syndrome), hyperglycemia, and injection site reactions (injection site erythema, pruritus, pain, urticaria, irritation, swelling, and hemorrhage).

Adverse reactions that occurred more frequently with EGRIFTA relative to placebo and had an incidence ≥1% during the first 26 weeks across all studies are presented in Table 1.

Table 1. Adverse Reactions Reported in ≥ 1% and More Frequent in EGRIFTA –treated than Placebo Patients during the 26-Week Phase (Combined Studies)
Preferred Term | Placebo (N=263) | EGRIFTA (N=543)
Injection site reaction* Arthralgia Pain in extremity Myalgia Edema peripheral Paresthesia Hypoesthesia Rash Dyspepsia Musculoskeletal pain Pain Pruritus Vomiting Musculoskeletal stiffness Blood creatine phosphokinase increased Carpal tunnel syndrome Joint swelling Muscle strain Night sweats Palpitations | 6 11 5 2 2 2 2 2 1 1 1 1 0 0 0 0 0 0 0 0 | 17 13 6 6 6 5 4 4 2 2 2 2 3 2 1 1 1 1 1 1
* Injection site reaction includes: Injection site erythema, Injection site pruritus, Injection site rash, Injection site urticaria, Injection site pain, Injection site swelling, Injection site irritation, Injection site hemorrhage.

In the EGRIFTA clinical trials, mean baseline HbA1c was 5.3% among patients in both the EGRIFTA and placebo groups. Patients receiving EGRIFTA had an increased risk of developing diabetes (HbA1c level ≥ 6.5%) compared with placebo (5% vs. 1%), with a hazard ratio of 3.3 (CI 1.4, 9.6).

7 DRUG INTERACTIONS

7.1 Cytochrome P450-Metabolized Drugs

Co-administration of tesamorelin with simvastatin, a CYP3A substrate had no significant impact on the pharmacokinetics profiles of simvastatin in healthy subjects [see Clinical Pharmacology (12.3)].

EGRIFTA SV stimulates GH production. Published data indicate that GH may modulate cytochrome P450 (CYP450) mediated antipyrine clearance. These data suggest that GH may alter the clearance of compounds known to be metabolized by CYP450 liver enzymes (e.g., corticosteroids, sex steroids, anticonvulsants, and cyclosporine). Monitor patients for potential interactions when administering EGRIFTA SV in combination with other drugs known to be metabolized by CYP450 liver enzymes.

7.2 Glucocorticoids

GH inhibits 11β-hydroxysteroid dehydrogenase type 1 (11βHSD-1), a microsomal enzyme required for conversion of cortisone to its active metabolite, cortisol, in hepatic and adipose tissue. EGRIFTA SV stimulates GH production; therefore, patients receiving glucocorticoid replacement for previously diagnosed hypoadrenalism may require an increase in maintenance or stress doses following initiation of EGRIFTA SV. Patients treated with cortisone acetate and prednisone may be affected more than others because conversion of these drugs to their biologically active metabolites is dependent on the activity of 11βHSD-1.

8 USE IN SPECIFIC POPULATIONS

8.1 Pregnancy

Risk Summary

EGRIFTA SV is contraindicated in pregnant women because modifying visceral adipose tissue offers no benefit in pregnant women and could result in fetal harm [see Clinical Considerations and Contraindications (4)]. Administration of tesamorelin acetate to rats during organogenesis resulted in hydrocephaly in offspring at a dose of approximately two and four times the clinical dose, based on measured drug exposure (AUC). If EGRIFTA SV is used during pregnancy, or if the patient becomes pregnant while taking it, discontinue EGRIFTA SV.

The estimated background risk of major birth defects and miscarriage for the indicated population is unknown. In the U.S. general population, the estimated background risk of major birth defects and miscarriage in clinically recognized pregnancies is 2% to 4% and 15% to 20%, respectively.

Clinical Considerations

Disease-associated maternal and/or embryo/fetal risk

During pregnancy, visceral adipose tissue increases due to normal metabolic and hormonal changes. Modifying pregnancy-associated physiologic changes in visceral adipose tissue with EGRIFTA SV offers no known benefit and could result in fetal harm.

Data

Animal Data

Tesamorelin acetate administration to rats during organogenesis and lactation resulted in hydrocephaly in offspring at a dose of approximately two and four times the clinical dose, respectively, based on measured drug exposure (AUC). Actual animal dose was 1.2 mg/kg. During organogenesis, lower doses approximately 0.1 to 1-times the clinical dose caused delayed skull ossification in rats. Actual animal doses were 0.1 to 0.6 mg/kg. No adverse developmental effects occurred in rabbits using doses up to approximately 500 times the clinical dose.

8.2 Lactation

Risk Summary

The Centers for Disease Control and Prevention recommend that HIV-infected mothers in the United States not breastfeed their infants to avoid risking postnatal transmission of HIV-1 infection. There are no data on the presence of tesamorelin in human milk, the effects on the breastfed child, or the effects on milk production. Because of both the potential for (1) HIV-1 infection transmission (in HIV-negative infants), (2) developing viral resistance (in HIV-positive patients), and (3) any possible adverse effects of tesamorelin, mothers should not breastfeed if they receive EGRIFTA SV.

8.4 Pediatric Use

The safety and effectiveness of EGRIFTA SV in pediatric patients have not been established.

In pediatric patients with open epiphyses, treatment with EGRIFTA SV may result in linear growth acceleration and excessive growth. EGRIFTA SV is not indicated for use in pediatric patients with open or closed epiphyses.

8.5 Geriatric Use

There is no information on the use of EGRIFTA SV in patients greater than 65 years of age.

11 DESCRIPTION

Tesamorelin is a human growth hormone-releasing factor (GRF) analog produced synthetically. It is comprised of the 44 amino acid sequence of human GRF and a hexenoyl moiety, a C6 chain with a double bond at position 3, attached to the tyrosine residue at the N-terminal part of the molecule. Tesamorelin is prepared as an acetate salt. The molecular formula of tesamorelin acetate is C221H366N72O67S • x C2H4O2 (x ≈ 7) and its molecular weight (as free base equivalent) is 5135.9 Da. The structural formula of tesamorelin acetate is:

EGRIFTA SV (tesamorelin) for injection is a sterile, white to off-white, preservative-free lyophilized powder for subcutaneous injection. Each single-dose vial of EGRIFTA SV contains tesamorelin 2 mg (equivalent to approximately 2.2 mg of tesamorelin acetate) and the following inactive ingredients: 0.78 mg histidine, USP, 20 mg mannitol, USP, 0.05 mg polysorbate 20, NF and 10 mg sucrose, NF. Hydrochloric acid may be used to adjust the pH. The pH of EGRIFTA SV is between 4.5 and 7.4. After reconstitution with 0.5 mL of Sterile Water for Injection, resultant concentration is 2 mg/0.5 mL and the solution is clear and colorless.

12 CLINICAL PHARMACOLOGY

12.1 Mechanism of Action

In vitro, tesamorelin binds and stimulates human GRF receptors with similar potency as the endogenous GRF [see Clinical Pharmacology (12.2)].

Growth hormone-releasing factor (GHRF), also known as growth hormone-releasing hormone (GHRH), is a hypothalamic peptide that acts on the pituitary somatotroph cells to stimulate the synthesis and pulsatile release of endogenous growth hormone (GH), which is both anabolic and lipolytic. GH exerts its effects by interacting with specific receptors on a variety of target cells, including chondrocytes, osteoblasts, myocytes, hepatocytes, and adipocytes, resulting in a host of pharmacodynamic effects. Some, but not all these effects, are primarily mediated by IGF-1 produced in the liver and in peripheral tissues.

12.2 Pharmacodynamics

Tesamorelin stimulates growth hormone secretion, and subsequently increases IGF-1 and IGFBP-3 levels. No clinically significant changes in the levels of other pituitary hormones, including thyroid-stimulating hormone (TSH), luteinizing hormone (LH), adrenocorticotropic hormone (ACTH) and prolactin, were observed in patients receiving EGRIFTA in clinical trials.

12.3 Pharmacokinetics

Absorption

The absolute bioavailability of tesamorelin after subcutaneous administration of a 2 mg dose of EGRIFTA (1 mg/vial formulation) was determined to be less than 4% in healthy adult subjects.

Single and multiple dose pharmacokinetics have been characterized in healthy subjects and HIV-infected patients without lipodystrophy using a 2 mg dose of EGRIFTA (1 mg/vial formulation). Tesamorelin mean extent of absorption (AUC) was 34% higher in HIV-infected patients than healthy subjects. Tesamorelin peak plasma concentration (Cmax) was similar in HIV-infected patients and healthy subjects. The median peak plasma tesamorelin concentration (Tmax) was 0.15 h in both populations.

Following single dose of subcutaneous administration of 1.4 mg of EGRIFTA SV (2 mg/vial formulation) in healthy subjects, the mean [coefficient of variation (CV)] AUC0-inf was 889.1 (57%) pg.h/mL. The mean (CV) Cmax value was 2956.1 (47%) pg/mL and the median Tmax was 0.15 h.

The systemic exposure (Cmax and AUCs) of tesamorelin is similar between the 1.4 mg dose of EGRIFTA SV (2 mg/vial formulation) and the 2 mg dose of EGRIFTA (1 mg/vial formulation).

Distribution

The mean volume of distribution (±SD) of tesamorelin following a single subcutaneous administration of the 1.4 mg dose of EGRIFTA SV (2 mg/vial formulation) was 4.8 ± 1.9 L/kg in healthy subjects.

Metabolism

No formal metabolism studies have been performed in humans.

Elimination

Mean elimination half-life (t1/2) of tesamorelin was 8 minutes in healthy subjects after single dose subcutaneous administration of the 1.4 mg of EGRIFTA SV (2 mg/vial formulation).

Specific Populations

Pharmacokinetics of tesamorelin in patients with renal or hepatic impairment, in pediatric patients, or in elderly patients has not been established.

Drug Interactions

Simvastatin

The effect of multiple dose administration of EGRIFTA on the pharmacokinetics of simvastatin and simvastatin acid was evaluated in healthy subjects. Co-administration with simvastatin (a CYP3A substrate) resulted in 8% decrease in extent of absorption (AUCinf) and 5% increase in rate of absorption (Cmax) of simvastatin. For simvastatin acid there was a 15% decrease in AUCinf and 1% decrease in Cmax [see Drug Interactions (7.1)].

Ritonavir

The effect of multiple dose administration of EGRIFTA on the pharmacokinetics of ritonavir was evaluated in healthy subjects. Co-administration with ritonavir resulted in 9% decrease in AUCinf and 11% decrease in Cmax of ritonavir [see Drug Interactions (7.1)].

12.6 Immunogenicity

The observed incidence of anti-drug antibodies is highly dependent on the sensitivity and specificity of the assay. Differences in assay methods preclude meaningful comparisons of the incidence of anti-drug antibodies in the studies described below with the incidence of the anti-drug antibodies in other studies, including those of EGRIFTA SV or other growth hormone-releasing factor analog.

In the clinical trials with the EGRIFTA 1 mg/vial formulation, anti-tesamorelin IgG antibodies were detected in 50% of patients who received EGRIFTA for 26 weeks and 47% of patients who received EGRIFTA for 52 weeks. In the subset of patients with hypersensitivity reactions, anti-tesamorelin IgG antibodies were detected in 85%. Cross-reactivity to endogenous growth hormone-releasing hormone (GHRH) was observed in approximately 60% of patients who developed anti-tesamorelin antibodies. Patients with and without anti-tesamorelin IgG antibodies had similar mean reductions in visceral adipose tissue (VAT) and IGF-1 response. In a group of patients who had antibodies to tesamorelin after 26 weeks of treatment (56%) and were re-assessed 6 months later, after stopping EGRIFTA treatment, 18% were still antibody positive.

Neutralizing antibodies to tesamorelin and human GHRH (hGHRH) were detected in vitro at Week 52 in 10% and 5% of EGRIFTA-treated patients, respectively. Changes in VAT and IGF-1 levels in patients with or without in vitro neutralizing antibodies were comparable.

13 NONCLINICAL TOXICOLOGY

13.1 Carcinogenesis, Mutagenesis, Impairment of Fertility

Life-time carcinogenicity studies in rodents have not been conducted with tesamorelin acetate. No potential mutagenicity of tesamorelin acetate was revealed in a battery of tests including induction of gene mutations in bacteria (the Ames test), gene mutations in mammalian cells grown in vitro (hamster CHOK1 cells), and chromosomal damage in intact animals (bone marrow cells in mice). There was no effect on fertility in male or female rats following administration of tesamorelin acetate at doses up to 0.6 mg/kg (approximately equal to clinical exposure) for 28 days in males or 14 days in females.

14 CLINICAL STUDIES

The safety and effectiveness of EGRIFTA SV (2 mg/vial formulation) has been established based on adequate and well controlled studies with EGRIFTA (1 mg/vial formulation), as well as a demonstration of comparable bioavailability between the 1.4 mg EGRIFTA SV dose (2 mg/vial formulation) and the 2 mg EGRIFTA dose (1 mg/vial formulation) [see Clinical Pharmacology (12.3)].

Two multicenter, randomized, double-blind, placebo-controlled studies were conducted in HIV-infected patients with lipodystrophy and excess abdominal fat (abdominal lipohypertrophy). Study 1 and Study 2 consisted of a 26-week Main Phase and a 26-week Extension Phase, respectively. Main inclusion criteria were age 18 to 65 years, a waist circumference ≥95 cm (37.4 inches) and a waist-to-hip ratio ≥0.94 for men and ≥94 cm (37.0 inches) and ≥0.88 for women, respectively, and fasting blood glucose (FBG) <150 mg/dL (8.33 mmol/L). Main exclusion criteria included BMI ≤ 20 kg/m^2, type 1 diabetes mellitus, type 2 diabetes mellitus, previous treatment with insulin or with oral hypoglycemic or insulin-sensitizing agents, history of malignancy, and hypopituitarism. Patients were on a stable anti-retroviral regimen for at least 8 weeks prior to randomization. Patients meeting the inclusion/exclusion criteria were randomized in a 2:1 ratio to receive a 2 mg dose of EGRIFTA (1 mg/vial formulation) or placebo subcutaneously daily for 26 weeks. The primary efficacy assessment for each of these studies was the percent change from baseline to Week 26 in visceral adipose tissue (VAT), as assessed by computed tomography (CT) scan at L4-L5 vertebral level. Secondary endpoints included changes from baseline in patient-reported outcomes related to body image, triglycerides, ratio of total cholesterol to HDL cholesterol, IGF-1 levels, and safety parameters. Other endpoints included changes from baseline in waist circumference, abdominal subcutaneous tissue (SAT), trunk fat, and lean body mass. In both studies, EGRIFTA-treated patients completing the 26-week treatment period were re-randomized to blinded therapy with either daily placebo or a 2 mg dose of EGRIFTA (1 mg/vial formulation) for an additional 26-week treatment period (Extension Phase) in order to assess maintenance of VAT reduction and to gather long-term safety data. For inclusion in the Extension Phase studies, subjects must have completed the Main Phase with FBG ≤ 150 mg/dL.

Main Phase (Baseline to Week 26):

Study 1 (NCT 00123253)

This study randomized 412 HIV-infected patients with lipodystrophy and excess abdominal fat to receive either a 2 mg dose of EGRIFTA (1 mg/vial formulation) (N=273) or placebo (N=137). At baseline for the two groups combined, mean age was 48 years; 86% were male; 75% were white, 14% were Black/African American, and 8% were Hispanic; mean weight was 90 kg; mean BMI was 29 kg/m^2; mean waist circumference was 104 cm; mean hip circumference was 100 cm; mean VAT was 176 cm^2; mean CD4 cell count was 606 cells/mm^3; 69% had undetectable viral load (<50 copies/mL); and 33.7% randomized to EGRIFTA and 36.6% randomized to placebo had impaired glucose tolerance, while 5.6% randomized to EGRIFTA and 6.7% randomized to placebo had diet-controlled diabetes mellitus. The twenty-six week completion rate in Study 1 was 80%.

Study 2 (NCT 00435136)

This study randomized 404 HIV-infected patients with lipodystrophy and excess abdominal fat to receive either a 2 mg dose of EGRIFTA (1 mg/vial formulation) (N=270) or placebo (N=126). At baseline for the two groups combined, mean age was 48 years; 84% were male; 77% were white, 12% were Black/African American, and 9% were Hispanic; mean weight was 88 kg; mean BMI was 29 kg/m^2; mean waist circumference was 105 cm; mean hip circumference was 100 cm; mean VAT was 189 cm^2; mean CD4 cell count was 592 cells/mm^3; 83% had undetectable viral load (<50 copies/mL); and 44% randomized to EGRIFTA and 40% randomized to placebo had impaired glucose tolerance, while 9% randomized to EGRIFTA and 10% randomized to placebo had diet-controlled type 2 diabetes mellitus. The twenty-six week completion rate in Study 2 was 74%.

Results for the Main Phases of Studies 1 and 2 are presented in Tables 2 and 3.

Table 2: Changes from Baseline to Week 26 in Visceral Adipose Tissue (cm^2) by Treatment Group (Intent-To-Treat Population with Last Observation Carried Forward)
MAIN PHASE (Baseline-Week 26)
 |  | Study 1 |  | Study 2
 |  | 2 mg EGRIFTA; (1 mg/vial); (N=273) | Placebo (N=137) | 2 mg EGRIFTA; (1 mg/vial); (N=270) | Placebo (N=126)
Baseline (cm^2) |  | 178 (77) | 171 (77) | 186 (87) | 195 (95)
Change (cm^2) |  | -27 | 4 | -21 | -0
Mean treatment difference (95% CI) |  | -31 (-39,-24) |  | -21 (-29,-12)
Mean change (%)^1 |  | -18 | 2 | -14 | -2
Mean treatment difference (95% CI)^1 |  | -20 (-24, -15) |  | -12 (-16, -7)
Baseline data are expressed as mean (SD); Change refers to least-squares mean (LSM); CI: confidence interval.
^1 Results derived from the statistical model: Ln(VAT Week 26/VAT Baseline) = Ln(VAT Baseline) + treatment group

Table 3: Changes from Baseline to Week 26 in IGF-1, IGFBP-3, Weight, and Waist Circumference by Treatment Group (Intent-To-Treat Population with Last Observation Carried Forward)
MAIN PHASE (Baseline-Week 26)
 |  | Study 1 |  | Study 2
 |  | 2 mg EGRIFTA (1 mg/vial) (N=273) | Placebo (N=137) | 2 mg EGRIFTA (1 mg/vial) (N=270) | Placebo (N=126)
IGF-1 (ng/mL) | Baseline | 161 (59) | 168 (75) | 146 (66) | 149 (59)
IGF-1 (ng/mL) | Change | 107 | -15 | 108 | 3
IGF-1 (ng/mL) | Mean treatment difference (95% CI) | 122 (101, 141) |  | 105 (85, 126)
IGFBP-3 (mg/L) | Baseline | 3 (1) | 3 (1) | 3 (1) | 3 (1)
IGFBP-3 (mg/L) | Change | 0.4 | -0.2 | 0.8 | -0.0
IGFBP-3 (mg/L) | Mean treatment difference (95% CI) | 0.6 (0.5, 0.8) |  | 0.8 (0.5, 1.0)
Weight (kg) | Baseline | 90 (14) | 90 (14) | 89 (14) | 87 (16)
Weight (kg) | Change | -0.4 | 0.0 | 0.5 | 0.3
Weight (kg) | Mean treatment difference (95% CI) | -0.4 (-1.3, 0.5) |  | 0.2 (-0.7, 1.3)
Waist circumference (cm) | Baseline | 104 (10) | 105 (9) | 105 (9) | 105 (9)
Waist circumference (cm) | Change | -3 (5) | -1 (4) | -2 (5) | -1 (5)
Waist circumference (cm) | Mean treatment difference (95% CI) | -2 (-2.8, -0.9) |  | -1 (-2.5, -0.3)
Baseline data are expressed as mean (SD); Change refers to least-squares mean (LSM); CI: confidence interval.

At Week 26, treatment with a 2 mg dose of EGRIFTA (1 mg/vial formulation) resulted in a reduction from baseline in mean trunk fat of 1.0 kg in Study 1 and 0.8 kg in Study 2, respectively (compared with an increase of 0.4 kg in Study 1 and of 0.2 kg in Study 2, respectively, in patients receiving placebo). Treatment with EGRIFTA resulted in an increase from baseline in mean lean body mass of 1.3 kg in Study 1 and of 1.2 kg in Study 2, respectively (compared with a decrease of 0.2 kg in Study 1 and of 0.03 kg in Study 2, respectively, in patients receiving placebo).

Patient Reported Outcomes

Patients rated the degree of distress associated with their belly appearance on a 9-point rating scale that was then transformed to a score from 0 (extremely upsetting and distressing) to 100 (extremely encouraging). A score of 50 indicated neutral (no feeling either way). A positive change from baseline score indicated improvement, i.e., less distress.

The cumulative distribution of response (change from baseline to 26 weeks) is shown in Figure 1 for both treatment groups. A curve shifted to the right on this scale indicates a greater percentage of patients reporting improvement.

Figure 1. Cumulative Distribution of Response for Belly Appearance Distress

Extension Phase (Weeks 26-52):

In the double-blind Extension Phase, patients on a 2 mg dose of EGRIFTA (1 mg/vial formulation) completing the 26-week Main Phase were re-randomized to receive a 2 mg dose of EGRIFTA (1 mg/vial formulation) or placebo.

Study 1 (NCT 00123253)

This study re-randomized 207 HIV-infected patients with lipodystrophy who completed a 2 mg dose of EGRIFTA (1 mg/vial formulation) treatment in the Main Phase to receive either EGRIFTA (N=154) or placebo (N=50) for an additional 26-week duration (3:1 randomization ratio). At baseline (Week 26) for the two groups combined, mean age was 48 years; 88% were male; 78% were white, 12% were Black/African American, and 8% were Hispanic; mean weight was 90 kg; mean BMI was 29 kg/m^2; mean waist circumference was 102 cm; mean hip circumference was 100 cm; mean VAT was 145 cm^2; mean CD4 cell count was 639 cells/mm3; 68% had undetectable viral load (<50 copies/mL); and for those EGRIFTA-treated patients completing the 26-week treatment period that were re-randomized to EGRIFTA (T-T group) or re-randomized to placebo, 37% and 32%, respectively, had impaired glucose tolerance, while 2% re-randomized to EGRIFTA and 6% re-randomized to placebo had diet-controlled type 2 diabetes mellitus. The completion rate for patients randomized into the extension phase of Study 1 was 83%.

Study 2 (NCT 00435136)

This study re-randomized 177 HIV-infected patients with lipodystrophy who completed EGRIFTA treatment in the Main Phase to receive either a 2 mg dose of EGRIFTA (1 mg/vial formulation) (N=92) or placebo (N=85) for an additional 26-week duration (1:1 randomization ratio). At baseline (Week 26) for the two groups combined, mean age was 48 years; 90% were male; 84% were white, 9% were Black/African American, and 7% were Hispanic; mean weight was 89 kg; mean BMI was 28 kg/m^2; mean waist circumference was 105 cm; mean hip circumference was 100 cm; mean VAT was 172 cm^2; mean CD4 cell count was 579 cells/mm^3; 82% had undetectable viral load (<50 copies/mL); and for those EGRIFTA-treated patients completing the 26-week treatment period that were re-randomized to EGRIFTA (T-T group) or re-randomized to placebo, 49% and 51%, respectively, had impaired glucose tolerance, while 4% re-randomized to EGRIFTA and 13% re-randomized to placebo had diet-controlled diabetes mellitus. The completion rate for patients randomized into the extension phase of Study 2 was 81%.

Results for the Extension Phases of Studies 1 and 2 are presented in Tables 4 and 5.

Table 4: Changes from Week 26 Baseline to Week 52 in Visceral Adipose Tissue (cm^2) by Treatment Group (Intent-To-Treat Population with Last Observation Carried Forward)
EXTENSION PHASE (Week 26-52)
 | Study 1 |  | Study 2
 | T-T^1 (Week 26-52) (N=154) | T-P^2 (Week 26-52) (N=50) | T-T^1 (Week 26-52) (N=92) | T-P^2 (Week 26-52) (N=85)
Week 26 (cm^2) | 145 (72) | 144 (72) | 166 (89) | 177 (88)
Change (cm^2) | 3 | 25 | -11 | 24
Mean treatment difference (95% CI) | -22 (-34, -10) |  | -35 (-48, -22)
Mean change (%)^3 | 0 | 22 | -5 | 16
Mean treatment difference (95% CI)^3 | -17 (-24, -10) |  | -18 (-24, -11)
Week 26 baseline data are expressed as mean (SD). Change refers to least-squares mean (LSM); CI: confidence interval.
^1T-T = tesamorelin for Weeks 0-26 and tesamorelin for Weeks 26-52
^2T-P = tesamorelin for Weeks 0-26 and placebo for Weeks 26-52
^3Results derived from the statistical model: Ln(VAT Week 52/Week 26) = Ln(Week 26 VAT) + treatment group

Figure 2 shows the percent change in VAT from baseline (Week 0) over time until 52 weeks in completer patients.

Figure 2. Percent Change from Baseline in VAT over Time

Data in Figure 2 are expressed as mean values. T-T (tesamorelin to tesamorelin) refers to the group of patients who received tesamorelin for Weeks 0-26 and were re-randomized to tesamorelin for Weeks 26-52. T-P (tesamorelin to placebo) refers to the group of patients who received tesamorelin for Weeks 0-26 and were re-randomized to placebo for Weeks 26-52. P-T (placebo to tesamorelin) refers to the group of patients who received placebo for Weeks 0-26 and were switched to tesamorelin (treated open label) for Weeks 26-52.

Table 5: Changes from Week 26 Baseline to Week 52 in IGF-1, IGFBP-3, Weight, and Waist Circumference by Treatment Group (Intent-To-Treat Population with Last Observation Carried Forward)
EXTENSION PHASE (Weeks 26-52)
 |  | Study 1 |  | Study 2
 |  | T-T^1 (Week 26-52) (N=154) | T-P^2 (Week 26-52) (N=50) | T-T^1 (Week 26-52) (N=92) | T-P^2 (Week 26-52) (N=85)
IGF-1 (ng/mL) | Week 26 | 291 (124) | 281 (105) | 280 (134) | 269 (110)
IGF-1 (ng/mL) | Change | -59 | -137 | -25 | -135
IGF-1 (ng/mL) | Mean treatment difference (95% CI) | 78 (50, 106) |  | 110 (87, 134)
IGFBP-3 (mg/L) | Week 26 | 3 (1) | 3 (1) | 3 (1) | 3 (1)
IGFBP-3 (mg/L) | Change | -0.2 | -0.5 | -0.3 | -0.9
IGFBP-3 (mg/L) | Mean treatment difference (95% CI) | 0.3 (-0.0, 0.6) |  | 0.6 (0.3, 0.9)
Weight (kg) | Week 26 | 89 (14) | 92 (17) | 89 (13) | 90 (14)
Weight (kg) | Change | 0.2 | 0.6 | -0.5 | 0.1
Weight (kg) | Mean treatment difference (95% CI) | -0.4 (-2, 1) |  | -0.6 (-2, 1)
Waist circumference (cm) | Week 26 | 101 (10) | 102 (12) | 101 (9) | 103 (11)
Waist circumference (cm) | Change | -0.2 | 2.4 | -1.1 | 0.2
Waist circumference (cm) | Mean treatment difference (95% CI) | -2.6 (-4, -1) |  | -1.3 (-2, 0)
Week 26 baseline data are expressed as mean (SD); Change refers to least-squares mean (LSM); CI: confidence interval.
^1T-T = tesamorelin for Week 0-26 and tesamorelin for Week 26-52
^2T-P = tesamorelin for Week 0-26 and placebo for Week 26-52

Patients treated with a 2 mg dose of EGRIFTA (1 mg/formulation) for 52 weeks (T-T group) showed no change between Weeks 26 and 52 in mean trunk fat (increase of 0.1 kg in Study 1 and decrease of 0.5 kg in Study 2, respectively, compared with an increase of 1.4 kg in patients in the T-P group in Study 1 and an increase of 1.09 kg in Study 2, respectively) nor was there a change from Week 26 baseline in mean lean body mass (decrease of 0.1 kg in Study 1 and increase of 0.1 kg in Study 2, respectively, compared with a decrease of 1.8 kg in patients in the T-P group in Study 1 and a decrease of 1.7 kg in Study 2, respectively).

16 HOW SUPPLIED/STORAGE AND HANDLING

EGRIFTA SV (tesamorelin) for injection is supplied as a white to off-white lyophilized powder in a 2 mg single-dose vial with a diluent of 10 mL vial of Sterile Water for Injection.

EGRIFTA SV (NDC 62064-241-30) is available in a package comprised of two boxes, containing 30 (thirty) 2 mg single-dose vials of EGRIFTA SV in the Medication Box and 30 single-dose 10 mL bottles of Sterile Water for Injection diluent with a 30-day supply of disposable syringes and needles in the Injection Box.

Store EGRIFTA SV 2 mg vial at room temperature at 20°C to 25°C (68°F to 77°F); excursions permitted to 15°C to 30°C (59°F to 86°F) [See USP Controlled Room Temperature]. Protect EGRIFTA SV from light by keeping in the original box until time of use. Store the Injection box (containing Sterile Water for Injection, syringes and needles) at room temperature at 20°C to 25°C (68°F to 77°F).

17 PATIENT COUNSELING INFORMATION

Advise the patient to read the FDA-approved patient labeling (Patient Information and Instructions for Use).

Increased Risk of Malignancy

Inform patients about the increased background risk of malignancies in HIV-positive patients and for patients with a history of neoplasms, inform them about the risk of malignancy reoccurrence [see Warnings and Precautions (5.1)].

Elevated IGF-1 Levels

Inform patients that treatment with EGRIFTA SV increases IGF-1 levels and that they will need periodic monitoring of their IGF-1 levels [see Warnings and Precautions (5.2)].

Fluid Retention

Inform patients that treatment with EGRIFTA SV may cause fluid retention, resulting in adverse reactions including edema, arthralgia, and carpal tunnel syndrome [see Warnings and Precautions (5.3)].

Glucose Intolerance or Diabetes Mellitus

Inform patients that treatment with EGRIFTA SV may result in glucose intolerance or diabetes mellitus. Advise patients that they will need to be monitored to see if impaired glucose tolerance or diabetes mellitus develops, and that if they have pre-existing diabetes mellitus, they may need adjustments to their anti-diabetic medications [see Warnings and Precautions (5.4)].

Hypersensitivity Reactions

Inform patients that hypersensitivity reactions (e.g., rash, urticaria) may occur during treatment with EGRIFTA SV. Advise patients to seek prompt medical attention and to immediately discontinue treatment with EGRIFTA SV if a reaction occurs [see Warnings and Precautions (5.5)].

Injection Site Reactions

Inform patients that injection site reactions may occur with EGRIFTA SV, including injection site erythema, pruritus, pain, irritation, and bruising. Advise patients to rotate the site of injection to reduce the risk of injection site reactions [see Warnings and Precautions (5.6)].

Pregnancy

Advise women to discontinue EGRIFTA SV if pregnancy occurs, as the drug offers no known benefit to pregnant women and could result in fetal harm [see Contraindications (4) and Use in Specific Populations (8.1)].

Lactation

Because of both the potential for HIV-1 infection transmission and serious adverse reactions in nursing infants, mothers receiving EGRIFTA SV should be instructed not to breastfeed [see Use in Specific Populations (8.2)].

Administration

Counsel patients that they should never share an EGRIFTA SV syringe with another person, even if the needle is changed. Sharing of syringes or needles between patients may pose a risk of transmission of infection.

EGRIFTA SV® is a registered trademark of Theratechnologies Inc.

Manufactured by Theratechnologies Inc., 2015 Peel Street, Suite 1100, Montréal, Québec, Canada H3A 1T8

US License No. 2091 for Theratechnologies Inc.

PATIENT INFORMATION

EGRIFTA SV® (eh-GRIF-tuh ESS-vee)

(tesamorelin) for injection

for subcutaneous use

2 mg vial

Read the Patient Information that comes with EGRIFTA SV before you start to take EGRIFTA SV and each time you get a refill. There may be new information. This leaflet does not take the place of talking to your healthcare provider about your medical condition or your treatment.

What is EGRIFTA SV?

- EGRIFTA SV is an injectable prescription medicine used to reduce the excess stomach-area (abdominal) fat in HIV-infected adult patients with lipodystrophy. EGRIFTA SV is a growth hormone-releasing factor (GHRF).

The long-term safety of EGRIFTA SV on the heart and blood vessels (cardiovascular) is not known.

EGRIFTA SV is not for weight loss management.

It is not known whether taking EGRIFTA SV helps improve how well you take (compliance with) antiretroviral medicines.

It is not known if EGRIFTA SV is safe and effective in children.

EGRIFTA SV is not recommended to be used in children with open or closed bone growth plates (epiphyses).

Who should not use EGRIFTA SV?

Do not use EGRIFTA SV if you:

- have a pituitary gland tumor, have had pituitary gland surgery, have other problems related to your pituitary gland, or have had radiation treatment to your head or a head injury.
- have active cancer. Any previous cancer should be inactive and any previous cancer treatment should be complete before starting EGRIFTA SV.
- are allergic to tesamorelin or any of the ingredients in EGRIFTA SV. See the end of this leaflet for a complete list of ingredients in EGRIFTA SV.
- are pregnant or plan to become pregnant. EGRIFTA SV can harm your unborn baby. If you become pregnant, stop using EGRIFTA SV and talk with your healthcare provider.

What should I tell my healthcare provider before using EGRIFTA SV?

Before using EGRIFTA SV, tell your healthcare provider about all of your medical conditions, including if you:

- have or have had cancer.
- have problems with your blood sugar or diabetes. Some people with diabetes who use EGRIFTA SV may develop or may have worsening eye problems.
- have scheduled heart or stomach surgery.
- have breathing problems.
- are breastfeeding or plan to breastfeed. It is not known if EGRIFTA SV passes into your breast milk. The Centers for Disease Control and Prevention (CDC) recommends that HIV-infected mothers not breastfeed to avoid the risk of passing HIV infection to your baby. Talk with your healthcare provider about the best way to feed your baby if you are using EGRIFTA SV.

Tell your healthcare provider about all the medicines you take, including prescription and over-the-counter medicines, vitamins, and herbal supplements.

How should I use EGRIFTA SV?

- Read the detailed “Instructions for Use” that comes with EGRIFTA SV before you start using it. Your healthcare provider will show you how to inject EGRIFTA SV.
- Use EGRIFTA SV exactly as your healthcare provider tells you to use it.
- Inject EGRIFTA SV under the skin (subcutaneously) of your stomach-area (abdomen).
- Change (rotate) the injection site on your stomach-area with each dose. Do not inject EGRIFTA SV into scar tissue, bruises or your belly button.
- Do not share your EGRIFTA SV syringe or needles with other people, even if the needle has been changed. You may give other people a serious infection or get a serious infection from them.

What are the possible side effects of EGRIFTA SV?

EGRIFTA SV may cause serious side effects, including:

- increase risk of new cancer in HIV positive patients or your cancer coming back (reactivation). Stop using EGRIFTA SV if any cancer symptoms come back.
- increased levels of your insulin-like growth factor-1 (IGF-1). Your healthcare provider will do blood tests to check your IGF-1 levels while you are taking EGRIFTA SV.
- swelling (fluid retention). EGRIFTA SV can cause swelling in some parts of your body. Call your healthcare provider if you have swelling, an increase in joint pain or pain or numbness in your hands or wrist (carpal tunnel syndrome). Joint pain and swelling of your arms, hands, legs and feet are common side effects of EGRIFTA SV, but may sometimes be serious.
- increase in blood sugar (glucose) or diabetes. Your healthcare provider will check your blood sugar before you start taking EGRIFTA SV and during your treatment with EGRIFTA SV.
- serious allergic reaction. Some people using EGRIFTA SV may have an allergic reaction. Stop using EGRIFTA SV and get emergency medical help right away if you have any of the following symptoms:

○ a rash over your body

○ shortness of breath or trouble breathing

○ hives

○ fast heartbeat

○ itching

○ swelling of your face or throat

○ feeling of faintness or fainting

○ reddening or flushing of the skin

- injection site reactions. Injection site reactions are a common side effect of EGRIFTA SV, but may sometimes be serious. Change (rotate) your injection site to help lower your risk for injection site reactions. Call your healthcare provider for medical advice if you have any of the following symptoms around the area of the injection site:

○ redness

○ irritation

○ swelling

○ itching

○ bruising or bleeding

○ pain

○ rash

- increased risk of death in people who have critical illnesses because of heart or stomach surgery, trauma or serious breathing (respiratory) problems has happened when taking certain amounts of growth hormone.

The most common side effects of EGRIFTA SV include:

• pain in legs and arms

• muscle pain

These are not all the possible side effects of EGRIFTA SV. For more information, ask your healthcare provider or pharmacist.

Call your doctor for medical advice about side effects. You may report side effects to FDA at 1-800- FDA-1088.

You may also report side effects to toll-free at 1-833-23THERA (1-833-238-4372).

How should I store EGRIFTA SV 2 mg vials, Sterile Water for Injection, syringes and needles?

- You will be given two boxes from the pharmacy when you get your prescription of EGRIFTA SV:
  o Store the 2 mg EGRIFTA SV vials in the Medication Box they come in, at room temperature at 20°C to 25°C (68°F to 77°F).
  o Store the Sterile Water for Injection, syringes and needles that come in the Injection Box at room temperature at 20°C to 25°C (68°F to 77°F).
- Keep EGRIFTA SV vials out of the light.
- After mixing, use EGRIFTA SV right away. Throw away any unused EGRIFTA SV after mixing.
- Do not store, freeze or refrigerate EGRIFTA SV after it has been mixed with the Sterile Water.
- Throw away any Sterile Water for Injection left in the bottle after use.
- Do not use EGRIFTA SV after the expiration date (EXP) printed on the carton and vial labels.

Keep EGRIFTA SV and all medicines out of the reach of children.

General information about the safe and effective use of EGRIFTA SV.

Medicines are sometimes prescribed for purposes other than those listed in a Patient Information leaflet. Do not use EGRIFTA SV for a condition for which it was not prescribed. Do not give EGRIFTA SV to other people, even if they have the same symptoms you have. It may harm them.

You can ask your healthcare provider or pharmacist for information about EGRIFTA SV that is written for health professionals.

What are the ingredients in EGRIFTA SV?

Active ingredient: tesamorelin (as an acetate salt)
Inactive ingredients: histidine, hydrochloric acid, mannitol, polysorbate 20, sucrose
EGRIFTA SV does not contain any preservative.

Manufactured by Theratechnologies Inc., 2015 Peel Street, Suite 1100, Montréal, Québec, Canada H3A 1T8 US License No. 2091 for Theratechnologies Inc.

For more information about EGRIFTA SV, go to www.EGRIFTASV.com or call toll-free at 1-833-23THERA (1-833-238-4372).

This Patient Information has been approved by the U.S. Food and Drug Administration Revised: 03/2024

Instructions for Use

EGRIFTA SV® (eh-GRIF-tuh ESS-vee)
(tesamorelin)
for injection
for subcutaneous use

This Instructions for Use contains step-by-step information on how to use the 2 mg vial of EGRIFTA SV. Each 2 mg vial of EGRIFTA SV must be mixed with 0.5 mL of the Sterile Water for Injection provided in the Injection Box given to you by the pharmacy. Use only one EGRIFTA SV 2 mg vial from the Medication Box to prepare your dose. The recommended dose of EGRIFTA SV is 1.4 mg (0.35 mL).

Be sure that you read, understand, and follow this Instructions for Use before using EGRIFTA SV. Your healthcare provider should show you how to mix and inject EGRIFTA SV before you inject it for the first time. Ask your healthcare provider if you have any questions.

Keep this Instructions for Use in case you need to look at it again later.

Important information for use of EGRIFTA SV

- Do not use a syringe or needle more than 1 time.
- Do not share your syringe or needles with other people, even if the needle has been changed. You may give other people a serious infection, or get a serious infection from them.
- If you are missing any supplies from the boxes given to you by the pharmacy or if any of the supplies look damaged, call your pharmacist or contact toll-free at 1-833-23THERA (1-833-238-4372) right away.

Preparing for your EGRIFTA SV injection

Step 1: Find a well-lit, clean, and flat surface, such as a table.

Step 2: Gather your supplies:

- Medication Box that contains 30 EGRIFTA SV 2 mg single-dose vials
- Injection Box that contains the following:
  - 30 single-dose 10 mL bottles of Sterile Water for Injection, used for mixing
  - 60 sterile 1 mL syringes
  - 60 sterile 1" 20-gauge needles, used for mixing
  - 30 sterile ½” 30-gauge needles, used for injection
- Other Supplies Needed
  - Two alcohol pads
  - One sterile gauze
  - One adhesive bandage
  - Sharps disposal container or a puncture resistant container for throwing away used needles and syringes after you are done with them. (See “How should I dispose of the used syringes, needles, bottles and vials?”)

For each injection using EGRIFTA SV 2 mg vial you will need: (See Figure A)

Figure A

Step 3: Take out the following from the Injection Box:

- One Sterile Water for Injection bottle
- Two 1 mL syringes
- Two 1" 20-gauge needles used for mixing
- One ½" 30-gauge needle used for injection

Step 4: Take 1 vial of EGRIFTA SV 2 mg from the Medication Box.

Step 5: Prepare to use your supplies:

- Wash your hands with soap and water. Dry your hands with a clean towel.
- Take off the plastic caps from the EGRIFTA SV 2 mg vial and the Sterile Water for Injection bottle.
- Clean the rubber stoppers on the top of the EGRIFTA SV 2 mg vial and Sterile Water for Injection bottle with an alcohol pad.

How to mix EGRIFTA SV 2 mg vial

Step 1: Place a 1" 20-gauge needle used for mixing, with its protective needle cap in place, onto a 1 mL syringe. Hold the syringe firmly and twist the needle cap clockwise (to the right) until it closes securely. (See Figure B)

Figure B

Step 2: Carefully remove the protective needle cap by pulling it straight off. Do not twist the needle cap.
Insert the needle through the rubber stopper of the Sterile Water for Injection bottle. (See Figure C)

Figure C

Step 3: With the needle still in the Sterile Water for Injection bottle, turn the bottle and syringe upside down.
Pull back the plunger until the Sterile Water reaches the 0.5 mL mark on the syringe. (See Figure D)

Figure D

Step 4: Remove the syringe with needle attached from the Sterile Water bottle.Throw away the bottle containing the unused Sterile Water for Injection. (See “How should I dispose of the used syringes, needles, bottles and vials?”)

Insert the needle into the rubber stopper of the EGRIFTA SV 2 mg vial.

With the needle at a slight angle, slowly push the plunger of the syringe all the way down so that the Sterile Water goes down the inside wall of the EGRIFTA SV 2 mg vial instead of directly onto the powder to avoid foaming. (See Figure E)

Figure E

Step 5: Remove the needle from the EGRIFTA SV 2 mg vial (see Figure F) and throw away the syringe and needle. (See “How should I dispose of the used syringes, needles, bottles and vials?”)

Figure F

Step 6: Roll the EGRIFTA SV 2 mg vial gently in your hands for 30 seconds, until the Sterile Water and EGRIFTA SV powder are mixed well. Do not shake the vial. (See Figure G)

Figure G

Note:

- After mixing, the solution should look clear and colorless, with no particles in it.
- Do not use EGRIFTA SV if it looks cloudy, discolored, or if you see particles in it.
- Call your healthcare provider, pharmacist, or contact toll-free at 1-833-23THERA (1-833-238-4372) right away if the solution is cloudy, discolored, or contains particles.

Step 7: Place a new unused 1" 20-gauge needle used for mixing, with its protective needle cap in place, onto a new unused 1 mL syringe. Hold the syringe firmly and twist the needle cap clockwise (to the right) until it closes securely. (See Figure H)

Figure H

Step 8: Carefully remove the protective needle cap by pulling it straight off. Do not twist the needle cap.
Do not throw away the needle cap.
Insert the needle through the rubber stopper of the EGRIFTA SV 2 mg vial. (See Figure I)

Figure I

Step 9: With the needle still in the EGRIFTA SV 2 mg vial, turn the vial and syringe upside down.
Pull the syringe back until you see just the tip of the needle going through the rubber stopper.
Pull back on the plunger of the syringe until all of the liquid inside the vial is in the syringe. The medicine should be at around the 0.4 mL mark on the syringe. (See Figure J)

Figure J

Step 10: Remove the needle from the vial. (See Figure K)

Figure K

Step 11: Place the protective needle cap on its side on a clean flat surface. Without touching the needle, hold the syringe and slide the needle carefully into the needle cap. (See Figure L).

Figure L

Step 12: Push the protective needle cap all the way in or until it snaps shut (See Figure M). Do not touch the needle cap until it covers the needle completely.

Figure M

Step 13: With the protective needle cap securely on the needle, remove the needle by holding the syringe firmly and twisting the needle cap counterclockwise (to the left). (See Figure N)
Throw away the needle. (See “How should I dispose of the used syringes, needles, bottles and vials?”)

Figure N

Step 14: Place a ½" 30-gauge needle to be used for your injection, with its protective needle cap and pink needle shield in place, onto the syringe. Hold the syringe firmly and twist the needle cap and pink needle shield clockwise (to the right) until it closes securely. (See Figure O)

Figure O

Where do I inject EGRIFTA SV 2 mg vial?

Inject EGRIFTA SV into the stomach-area (abdomen). (See Figure P)

- Choose an injection site that is at least 2 inches (5 cm) away from your belly button. (See the shaded area in Figure P)
- Do not inject into areas with scar tissue or bruises.
- Do not inject into your belly button.
- Avoid areas with any hard bumps from previous injections.
- Rotate the site for each injection. This may help prevent bruising or irritation. You may want to write down the date and location of each daily injection to help you remember.

Figure P

How to inject your 1.4 mg dose of EGRIFTA SV

Do not remove the needle cap until you are ready to inject.

Step 1: Hold the syringe with the needle facing up. Pull the pink needle shield down away from the white protective needle cap.
Carefully remove the needle cap by pulling it straight off the needle. Do not twist the needle cap. (See Figure Q)
Do not touch the needle.

Figure Q

Step 2: Tap the syringe gently with your finger to force any air bubbles to rise to the top.
Slowly push up on the plunger to remove any air and bubbles and until the medicine in the syringe is at the 0.35 mL mark of the syringe. (See Figure R)

Figure R

Step 3: Clean the injection site you have selected with an alcohol pad and let it dry.
Hold the syringe in one hand. With your other hand, gently pinch a fold of skin at your cleaned injection site. Hold the skin between your thumb and fingers. (See Figure S)

Figure S

Step 4: Hold the syringe at a 90 degree angle to the skin.
With a quick, dart-like motion, insert the needle straight into the skin. Most of the needle should go beneath the skin. (See Figure T)

Figure T

Step 5: Remove your hand from the pinched area of skin after the needle is inserted. Be careful not to remove the needle from the skin.

Step 6: Slowly push the plunger of the syringe all the way down until all of the medicine in the syringe has been injected. (See Figure U)

Figure U

Pull the needle out of your skin. Be careful to pull the needle out at the same angle as it was inserted.

Step 7: While holding the syringe in one hand, gently press the pink needle shield against a hard, flat surface until you hear a “click” and the injection needle is covered by the pink needle shield. (See Figure V)

Figure V

- Apply pressure to the injection site with gauze for 30 seconds. If there is bleeding, apply an adhesive bandage to the site.
- Throw away the syringe. (See “How should I dispose of the used syringes, needles, bottles and vials?”)

How should I dispose of the used syringes, needles, bottles and vials?

- Do not recap the needle or remove the needle from the syringe after you inject EGRIFTA SV.
- Put your used EGRIFTA SV needles and syringes in a FDA-cleared sharps disposal container right away after use. Do not throw away (dispose of) loose needles and syringes in your household trash.
- If you do not have a FDA-cleared sharps disposal container, you may use a household container that is:
  - made of a heavy-duty plastic,
  - can be closed with a tight-fitting, puncture-resistant lid, without sharps being able to come out,
  - upright and stable during use,
  - leak-resistant, and
  - properly labeled to warn of hazardous waste inside the container.
- When your sharps disposal container is almost full, you will need to follow your community guidelines for the right way to dispose of your sharps disposal container. There may be state or local laws about how you should throw away used needles and syringes. For more information about safe sharps disposal, and for specific information about sharps disposal in the state that you live in, go to the FDA's website at: http://www.fda.gov/safesharpsdisposal .
- Do not dispose of your used sharps disposal container in your household trash unless your community guidelines permit this. Do not recycle your used sharps disposal container.
- If another person receives a needle stick with a used needle, that person should be told to contact a healthcare provider right away.
- Keep the sharps container away from children and pets.

If you have any questions, call your healthcare provider. You can call toll-free at 1-833-23THERA (1-833-238-4372) or visit the EGRIFTA SV website at: www.EGRIFTASV.com for more information.

How should I store EGRIFTA SV 2 mg vials, Sterile Water for Injection, syringes and needles?

- You will be given 2 boxes from the pharmacy when you get your prescription of EGRIFTA SV:
  - Store the 2 mg EGRIFTA SV vials in the Medication Box they come in, at room temperature between 68°F to 77°F (20°C to 25°C).
  - Store the Sterile Water for Injection, syringes and needles that come in the Injection Box at room temperature between 68°F to 77°F (20°C to 25°C).
- Keep EGRIFTA SV vials out of the light.
- After mixing, use EGRIFTA SV right away. Throw away any unused EGRIFTA SV after mixing.
- Do not store, freeze or refrigerate EGRIFTA SV after it has been mixed with the Sterile Water.
- Throw away any Sterile Water for Injection left in the bottle after use.
- Do not use EGRIFTA SV after the expiration date (EXP) printed on the carton and vial labels.

Keep EGRIFTA SV and all medicines out of the reach of children.

This Instructions for Use has been approved by the U.S. Food and Drug Administration.

EGRIFTA SV® is a registered trademark of Theratechnologies Inc.

Manufactured by: Theratechnologies Inc., 2015 Peel Street, Suite 1100, Montréal, Québec, Canada H3A 1T8 US Licence No. 2091 for Theratechnologies Inc.

Revised: 03/2024

PACKAGE LABEL

Principal Display Panel - Medication Box

MEDICATION BOX

(Box 1 of 2)

NDC 62064-241-30

2 mg/vial

Rx only

EGRIFTA SV®

(tesamorelin) for injection

2 mg/vial

For subcutaneous injection only

Important: Refer to Patient Instructions for Use

Use only 1 vial of EGRIFTA SV 2 mg to
prepare the recommended dose of 1.4 mg
(0.35 mL of the reconstituted solution).

READ BEFORE OPENING BOX:

This is the MEDICATION BOX – it contains 30 vials of
EGRIFTA SV 2 mg/vial and the Patient Instructions for Use.
You will also need the INJECTION BOX for EGRIFTA SV –
it contains syringes and other materials needed for
reconstitution and administration.

Protect
from light.
Keep in
original box.

Store at room
temperature at
20°C to 25°C
(68°F to 77°F)

EGRIFTA SV® is a registered
trademark of Theratechnologies Inc.

PACKAGE LABEL

Principal Display Panel - Injection Box

INJECTION BOX (Box 2 of 2)

For use only with EGRIFTA SV® 2 mg/vial
(tesamorelin) for injection 2 mg/vial

For mixing,
refer to Patient
Instructions for Use
included in the
EGRIFTA SV 2 mg/vial
Medication Box.

Rx only

READ BEFORE OPENING BOX

This is your INJECTION BOX for EGRIFTA SV (tesamorelin) for injection 2 mg/vial.

This box contains sterile syringes, Sterile Water for Injection USP, and materials
needed for injecting EGRIFTA SV.

Note this INJECTION BOX does NOT contain your EGRIFTA SV 2 mg/vial medication.

Before removing contents, make sure you also have the
EGRIFTA SV 2 mg/vial MEDICATION BOX.

Contents of INJECTION BOX:

a) 30 single-dose, 10 mL bottles of Sterile Water for Injection

b) 60 sterile 1mL syringes

c) 60 sterile 1" 20-gauge needles, used for mixing

d) 30 sterile ½" 30-gauge needles, used for injection

Store at
controlled room
temperature
20°C to 25°C
(68°F to 77°F)

Made in USA

Manufactured by: Theratechnologies Inc., 2015 Peel Street, Suite 1100, Montréal, Québec, Canada H3A 1T8 US Licence No. 2091 for Theratechnologies Inc.

Principal Display Panel - 2 mg Vial Label

2 mg/vial

EGRIFTA SV®

(tesamorelin) for injection

Rx only

STERILE

Store at
20°C to 25°C

(68° to 77°F)

For subcutaneous injection only

Each vial contains 2 mg of tesamorelin

Single-Dose Vial - Discard Unused Portion

Mfd. By Theratechnologies Inc. US License No. 2091